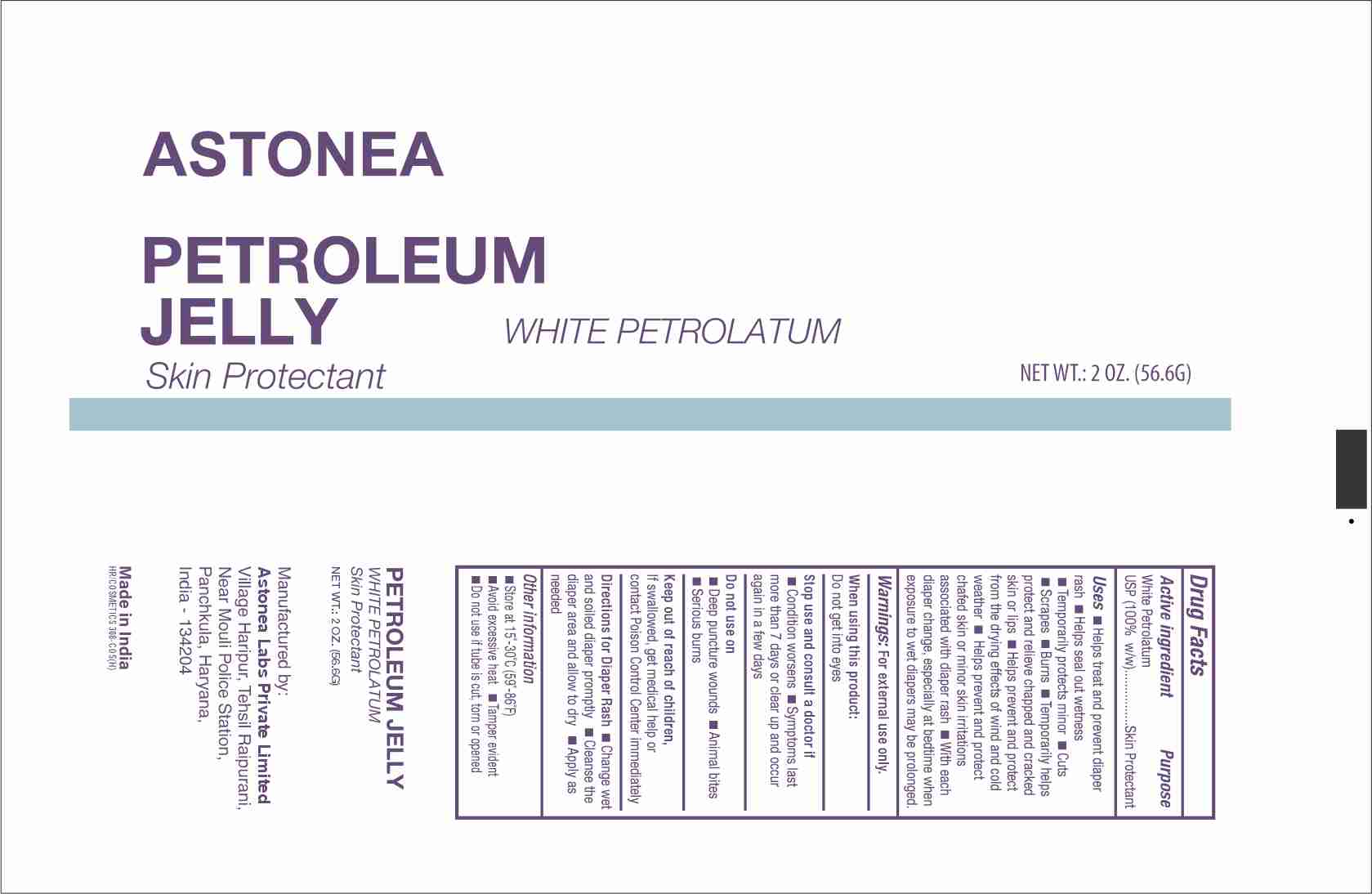 DRUG LABEL: ASTONEA PETROLATUM
NDC: 77338-211 | Form: OINTMENT
Manufacturer: ASTONEA LABS PRIVATE LIMITED
Category: otc | Type: HUMAN OTC DRUG LABEL
Date: 20240424

ACTIVE INGREDIENTS: PETROLATUM 1 g/1 g

ASTONEA PETROLATUM

Active Ingredient (in each gram)

White Petrolatum, USP, 100% w/w

Purpose

Skin Protectant

Uses

- Helps treat and prevent diaper rash
- Helps seal out wetness
- Temporarily protects minor cuts, scrapes and burns
- Temporarily helps protect and helps relieve chapped and cracked skin or lips
- Helps prevent and protect from the drying effects of wind and cold weather
- Helps prevent and protect from chafed skin or mionr skin irritations associated with diaper rash, with each diaper change, especially at bedtime when exposure to wet diapers may be prolonged

Directions

- Change wet and soiled diapers promptly
- Cleanse the diaper area and allow to dry
- Apply as needed

Warnings

For External Use Only.

Do not use on

- Deep or puncture wounds
- Animal bites
- Serious burns

Stop use and ask a doctor if

- The condition persists or gets worse
- Symptoms persists for more than 7 days or clear up and occur again within a few days.

Keep out of reach of children

If swallowed, get medical help or contact a Poison Control Center right away.

Other information

- Store at controlled room temperature 15o - 30oC(59o--86o F)
- Avoid excessive heat and humidity
- Tamper evident
- Do not use if packet is torn, cut or opened

When using this product

- Do not get into eyes

Inactive Ingredients

None